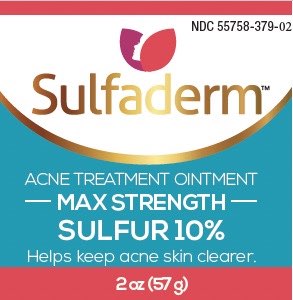 DRUG LABEL: Sulfaderm
NDC: 55758-379 | Form: OINTMENT
Manufacturer: Pharmadel LLC
Category: otc | Type: HUMAN OTC DRUG LABEL
Date: 20251204

ACTIVE INGREDIENTS: SULFUR 10 g/100 g
INACTIVE INGREDIENTS: WATER; CETOSTEARYL ALCOHOL; GLYCERYL MONOSTEARATE; METHYLPARABEN; MINERAL OIL; PARAFFIN; PETROLATUM; POLYETHYLENE GLYCOL, UNSPECIFIED; PROPYLPARABEN; SORBITAN MONOOLEATE; GLYCERIN

Sulfaderm Acne Treatment (WP)(DA)

Drug Facts

Active ingredient & Purpose

Active ingredient | Purpose
Sulfur 10% ........................ | Acne treatment

Uses

For the treatment of acne. Clears up acne:

- blemishes
- pimples
- blackheads
- whiteheads

Warnings

For external use only. Avoid contact with the eyes.

Do not use on

- broken skin
- large areas of the skin

When using this product

- skin irritation and dryness are more likely to occur if you use another topical acne medication at the same time. If irritation occurs, only use one topical acne medication at a time.
- apply only to areas with acne

If pregnant or breast feeding,

ask a health professional before use

Keep out of the reach of children.

If swallowed, get medical help or contact a Poison Control Center right away.

Directions

- cleanse the skin thoroughly before applying this product
- cover the entire affected area with a thin layer one to three times daily
- because excessive drying of the skin may occur, start with one application daily, then gradually increase to two or three times daily if needed or as directed by a doctor
- if bothersome dryness or peeling occurs, reduce application to once a day or every other day

Other information

- store between (59-86°F) 15-30°C
- don’t use if clear seal over cap is broken, torn, or missing

Inactive ingredients

cetyostearyl alcohol, glycerin, glyceryl monostearate, methylparaben, mineral oil, paraffin, petrolatum, propylparaben, polyethylene

glycol, sorbitan monooleate, water

Distributed by:

Pharmadel LLC

New Castle, DE 19720

+1-866-359-3478